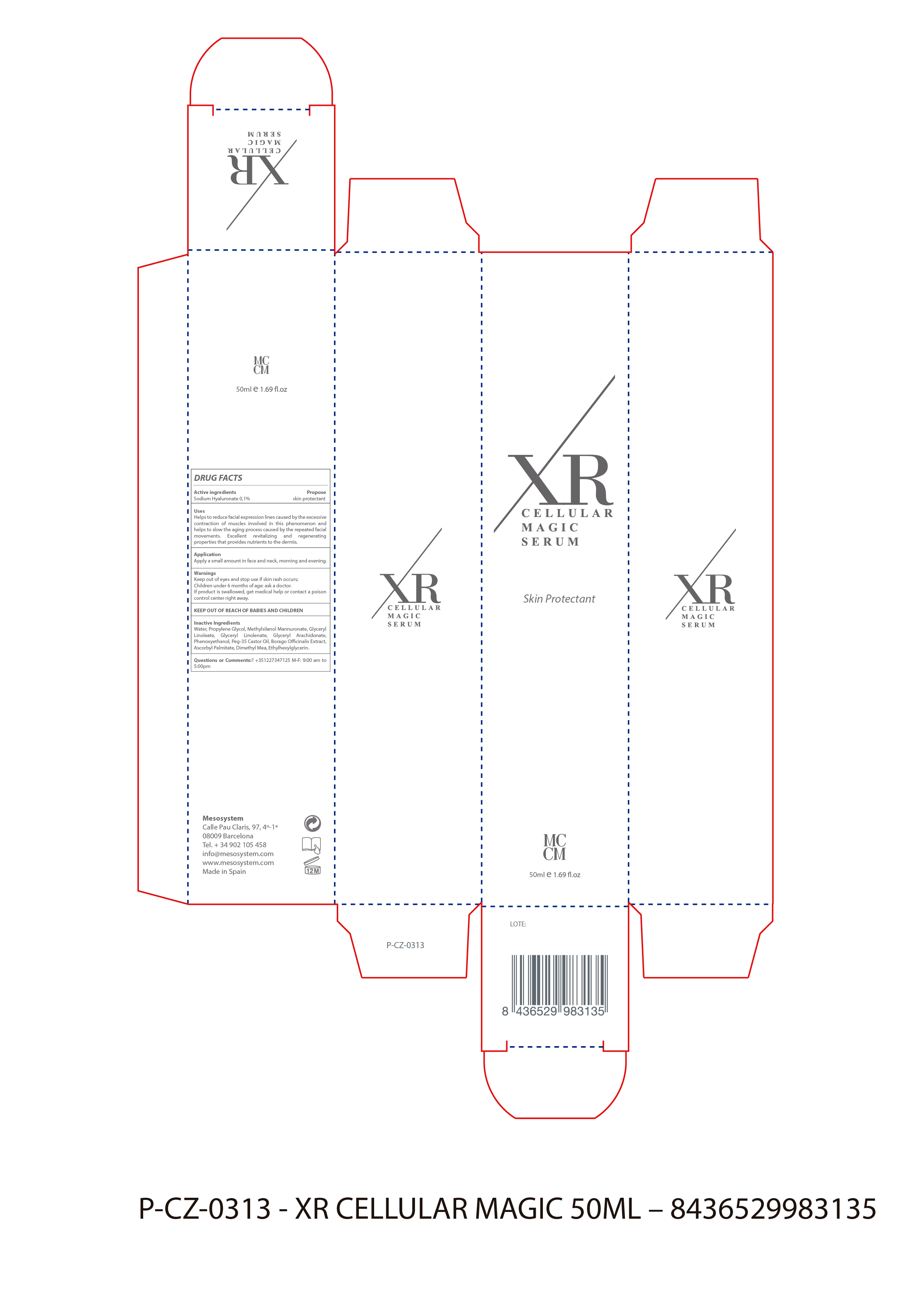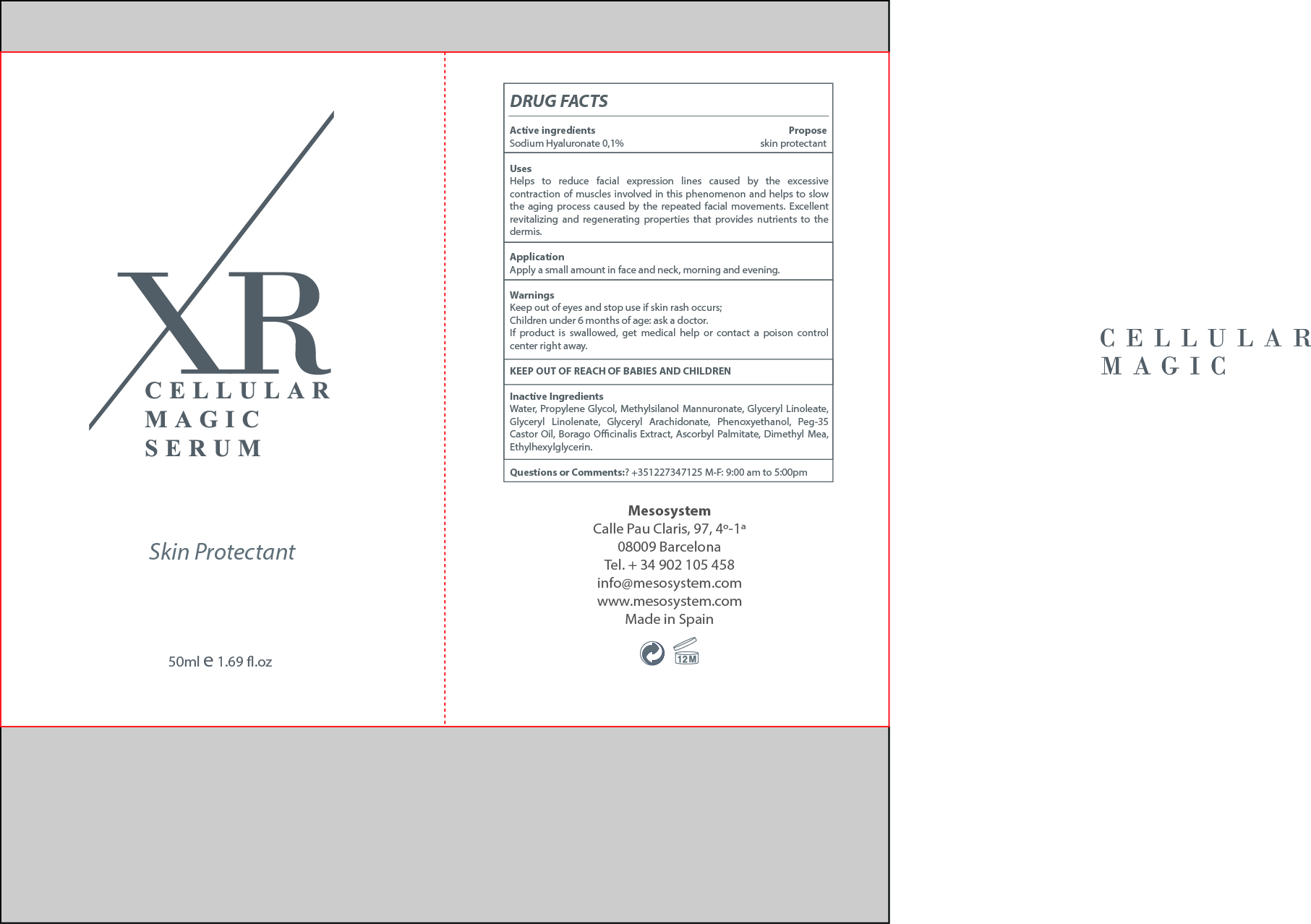 DRUG LABEL: XR CELLULAR MAGIC
NDC: 70663-008 | Form: GEL
Manufacturer: MESO SYSTEM S.A.
Category: otc | Type: HUMAN OTC DRUG LABEL
Date: 20161217

ACTIVE INGREDIENTS: HYALURONATE SODIUM 0.1 mg/1 mL
INACTIVE INGREDIENTS: POLYOXYL 35 CASTOR OIL 0.2 mg/1 mL; BORAGO OFFICINALIS FLOWER 0.2 mg/1 mL; ASCORBYL PALMITATE 0.1 mg/1 mL; DIPROPYLENE GLYCOL 10 mg/1 mL; SODIUM MANNURONATE METHYLSILANOL 5 mg/1 mL; WATER 80.3 mg/1 mL; PHENOXYETHANOL 0.9 mg/1 mL; PEG-30 GLYCERYL LINOLEATE 1 mg/1 mL; ETHYLHEXYLGLYCERIN 0.1 mg/1 mL; GLYCERYL ARACHIDONATE 1 mg/1 mL; GLYCERYL LINOLENATE 1 mg/1 mL; DEANOL 0.1 mg/1 mL

XR CELLULAR MAGIC

Warnings

Stop use and ask a Doctor if skin rash occurs

WARNINGS

- For external use only
- Stop use and ask a doctor if skin rash occur.s
- Avoid the product from entering your eyes
- Children under 6 months Ask a Doctor

USES

- Helps to reduce facial expression lines caused by the excessive contraction of muscles envolved in this phenomenos and
- helps to slow the aging process caused by the repeated facil movements. Excellent revitalizing and regenerating properties that provides nutrient to the dermis

- Keep out of the reach of chuldren.
- In case of overdose get medical help or Contact a Poison Control Center right away.

DIRECTIONS

- Apply a small amount in the face and neck, morning and evening

QUESTIONS OR COMMENTS ?

- +35 1227347125 M-F: 9:00 am to 5:00 pm

ACTIVE INGREDIENTS

Active Ingredients Purpose

Sodium Hyaluronate 0.1%....................................Skin Protectant

Inactive Ingredients

Water, Propylene Glycol, Methylsilanol Mannuronate, Glyceryl Linoleate, Glyceryl Linolenate, Glyceryl Arachidonate, Phenoxyethanol, Peg-35 Castor Oil, Borago Officinalis Extract, Ascorbyl Palmitate, Dimethyl Mea, Ethylhexylglycerin

INDICATIONS AND USAGE

Apply a small amount in the face and neck, morning and evening

PACKAGE LABEL

XR CELLULAR MAGIC

SKIN PROTECTANT